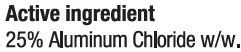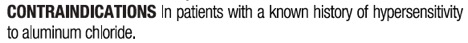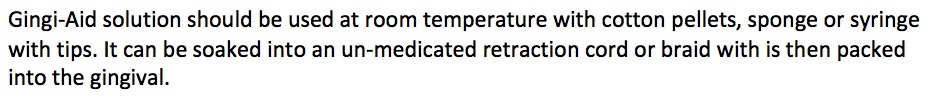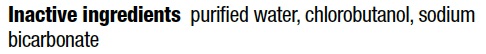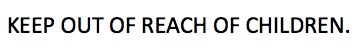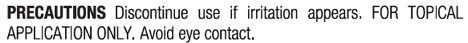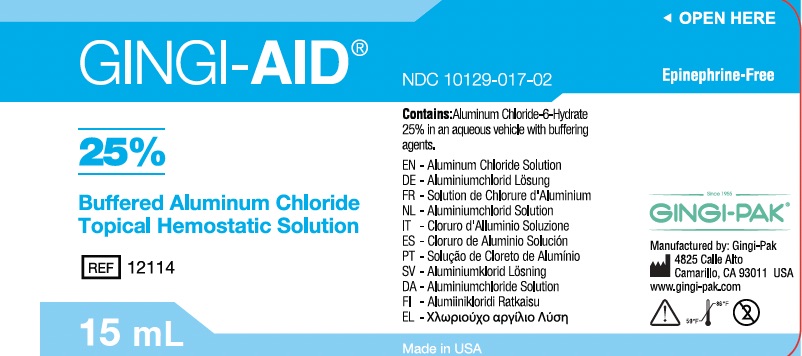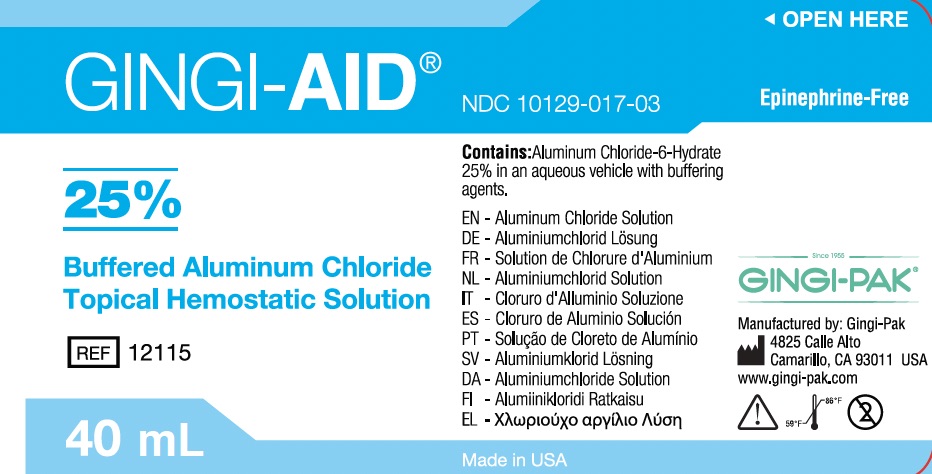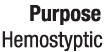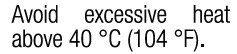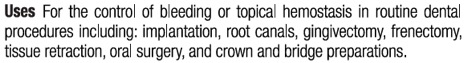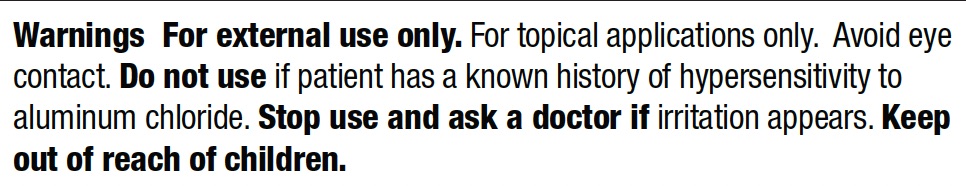 DRUG LABEL: Gingi-Aid Solution
NDC: 10129-017 | Form: SOLUTION
Manufacturer: Gingi-Pak a Division of the Belport
Category: otc | Type: HUMAN OTC DRUG LABEL
Date: 20220720

ACTIVE INGREDIENTS: ALUMINUM CHLORIDE 3.75 g/15 mL
INACTIVE INGREDIENTS: CHLOROBUTANOL 3 mg/15 mL

Gingi-Aid Solution